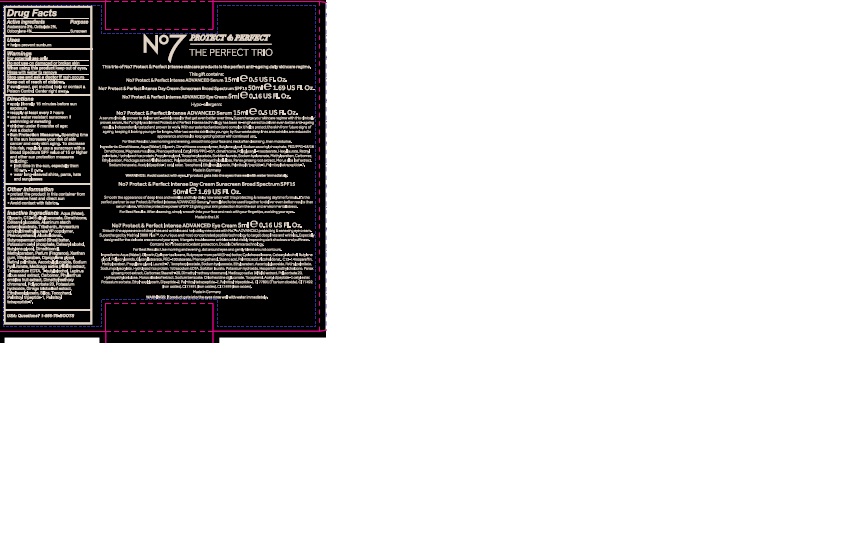 DRUG LABEL: No7 Protect and Perfect Intense Day Cream SPF 15
NDC: 11489-107 | Form: CREAM
Manufacturer: BCM Ltd
Category: otc | Type: HUMAN OTC DRUG LABEL
Date: 20160708

ACTIVE INGREDIENTS: AVOBENZONE 1.5 g/50 g; OCTOCRYLENE 2 g/50 g; OCTISALATE 1 g/50 g
INACTIVE INGREDIENTS: WATER; GLYCERIN; DIMETHICONE; CETEARYL GLUCOSIDE; ALUMINUM STARCH OCTENYLSUCCINATE; TRIBEHENIN; POTASSIUM CETYL PHOSPHATE; AMMONIUM ACRYLOYLDIMETHYLTAURATE/VP COPOLYMER; PHENOXYETHANOL; CETOSTEARYL ALCOHOL; SHEA BUTTER; BUTYLENE GLYCOL; METHYLPARABEN; DIMETHICONOL (40 CST); DIPROPYLENE GLYCOL; XANTHAN GUM; VITAMIN A PALMITATE; ASCORBYL GLUCOSIDE; MEDICAGO SATIVA LEAF; EDETATE SODIUM; TERT-BUTYL ALCOHOL; LUPINUS ALBUS SEED OIL; POLYSORBATE 20; CARBOMER 940; PHYLLANTHUS EMBLICA FRUIT; DIMETHYLMETHOXY CHROMANOL; POTASSIUM HYDROXIDE; GINKGO BILOBA LEAF OIL; ETHYLHEXYLGLYCERIN; TOCOPHEROL; PALMITOYL TETRAPEPTIDE-7; PALMITOYL TRIPEPTIDE-1

No7 Protect and Perfect Intense Day Cream Sunscreen Broad Spectrum SPF 15

Carton Active Ingredients Section

Active ingredients

Avobenzone 3%

Octisalate 2%

Octocrylene 4%

Uses

Uses - helps prevent sunburn

Warnings

For external use only

Do not use on damaged or broken skin

When using this product keep out of eyes. Rinse with water to remove.

Ask a doctor

Stop use and ask a doctor if rash occurs

Keep out of reach of children

If swallowed, get medical help or contact a Poison Control Center right away

Directions

Apply liberally 15 minutes before sun exposure

reapply at least every 2 hours

use a water resistant sunscreen if swimming or sweating

children under 6 months of age: Ask a doctor

Sun Protection Measures. Spending time in the sun increases your risk of skin cancer and early skin aging.

To decrease this risk, regularly use a sunscreen with a Broad Spectrum SPF value of 15 or higher and other sun protection measures including:

Limit time in the sun, especially from 10 a.m - 2 p.m.

wear long-sleeved shirts,pants,hats and sunglasses.

Storage

Other information

Protect the product in this container from excessive heat and direct sun

Avoid contact with fabrics

Inactive ingredients

Aqua(Water), Glycerin, C12-15 alkyl bezoate, Dimethicone, Cetearyl glucoside, Aluminum starch octenylsuccinate, Tribehenin, Ammonium acryloydimethyltaurate/VP copolymer, Phenoxyethanol, Alcohol denat, Butyrospermum parkii (Shea) butter, Potassium cetyl phosphate, Cetearyl alcohol, Butylene glycol, Dimethiconol, Methyparaben, Parfum(Fragrance) Xanthan gum, Ethylparaben, Dipropylene glycol, Retinyl palmitate, Ascorbyl glucoside, Sodium hyaluronate, Medicago sativa(Alfalfa) extract, Tetrasodium EDTA, T-butyl alcohol, Lupinus albus seed extract, Carbomer, Phyllanthus emblica fruit extract, Dimethylmethoxychromanol, Polysorbate 20, Potassium hydroxide, Ginkgo biloba leaf extract, Ethylhexyglycerin, silica, Tocopherol, Palmitoyl tripeptide-1, Palmitoyl tetrapeptide-7

PATIENT COUNSELING INFORMATION

Made in the UK

The Boots Company PLC Nottingham England NG2 3AA

Dist. by Boots Retail USA Inc. New York NY 10005

www.boots.com

Description section

No7 Protect and Perfect The Perfect Trio

This trio of No7 Protect and Perfect Intense skincare products is the perfect anti-ageing daily skincare regime.

This gift contains:

No7 Protect and Perfect Intense ADVANCED Serum 15ml e 0.5 US Fl.Oz.

No7 Protect and Perfect Intense Day Cream Sunscreen Broad Spectrum SPF 15 50ml e 1.69 Us Fl.Oz.

No7 Protect and Perfect Intense ADVANCED Eye Cream 5ml e 0.16 US Fl.Oz.

No7 Protect and Perfect Intense ADVANCED Serum 15ml e 0.5 US Fl.Oz.

A serum clinically proven to deliver anti-wrinkle results that get even better over time. Supercharge your skincare regime with this clinically proven serum. No7's highly acclaimed Protect and Perfect Intense technology has been re-engineered to delver even better anti-ageing results. Independently tested and proven to work. With our patented antioxidant complex it helps protect the skin from future signs of ageing, keeping it looking younger for longer. After two weeks skin looks younger, by four weeks deep lines and wrinkles are reduced in appearance and results keep getting better with continued use.

For Best Results : Use morning and evening, smooth into your face and neck after cleansing, then moisturise.

No7 Protect and Perfect Intense Day Cream Sunscreen Broad Spectrum SPF 15

50ml e 1.69 US Fl.Oz

Smooth the appearance of deep lines and wrinkles and help delay new ones with this protecting and renewing daytime formula.It's the perfect partner to our Protect and Perfect Intense ADVANCED Serum. Formulated to be used together to deliver even better results than serum alone. With the protective power of SPF 15 giving your skin protection from the sun and environmental stress.

For Best Results: After cleansing, simply smooth into your face and neck with your fingertips, avoiding your eyes.

No7 Protect and Perfect Intense ADVANCED Eye Cream 5ml e 0.16 US Fl.Oz.

Smooth the appearance of deep lines and wrinkles and help delay new ones with No7's ADVANCED protecting and renewing eye cream. Supercharge by Matrixyl 3000 Plus TM, our unique and most concentrated peptide technology to target deep lines and wrinkles. Especially designed for the delicate area around your eyes, it targets troublesome wrinkles whilst visibly improving dark shadows and puffiness.

Contains No7's best antioxidant protection, Double Defence technology.

For Best Results: Use morning and evening, dot around eyes and gently blend around contours.